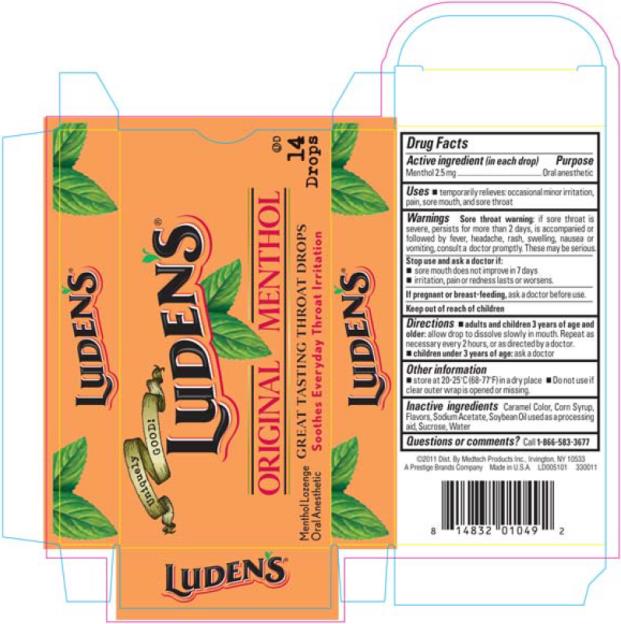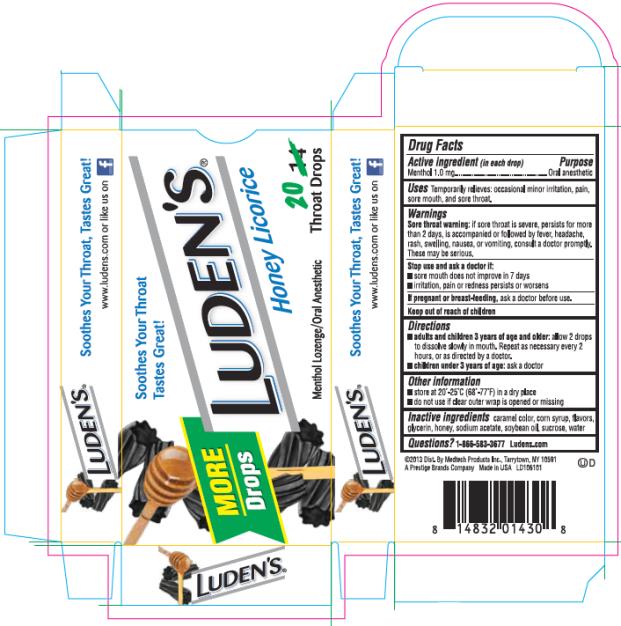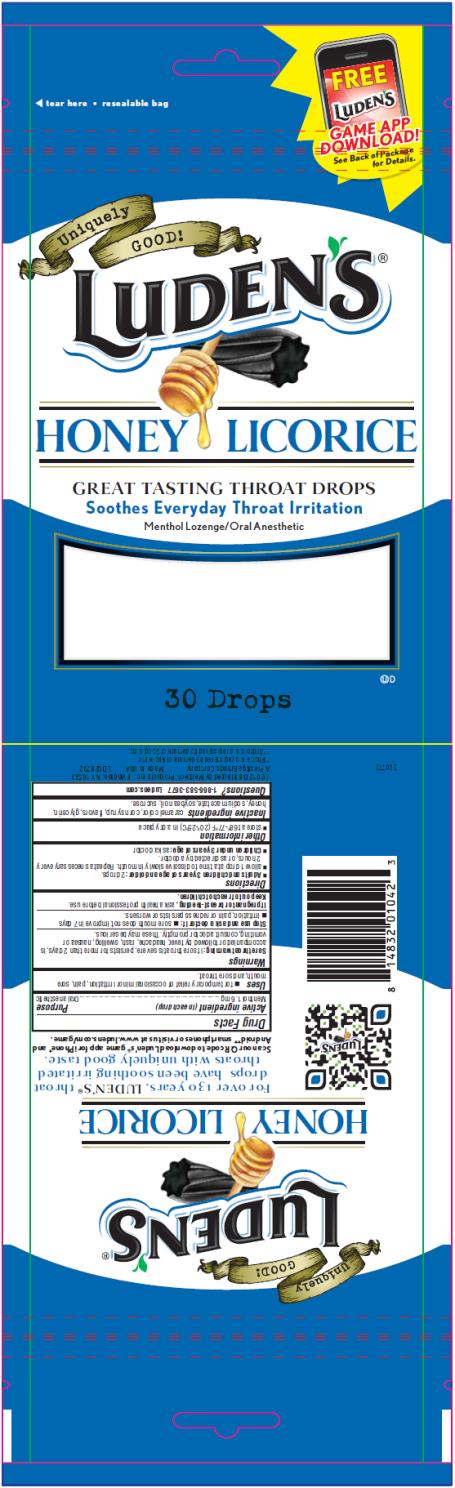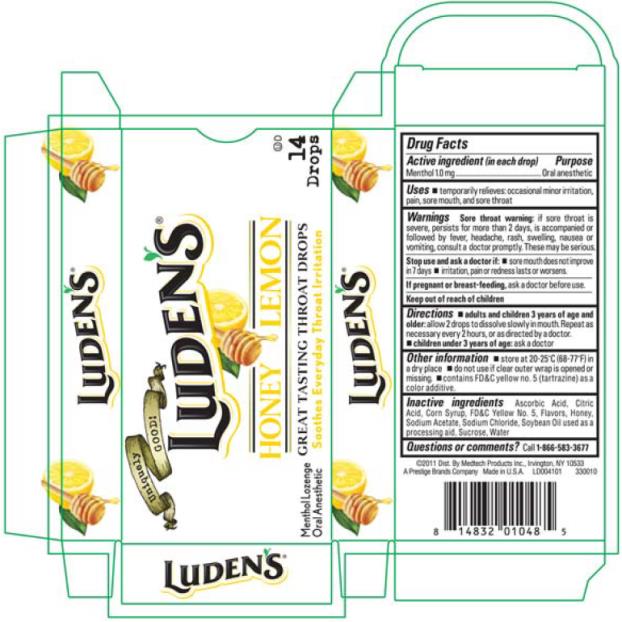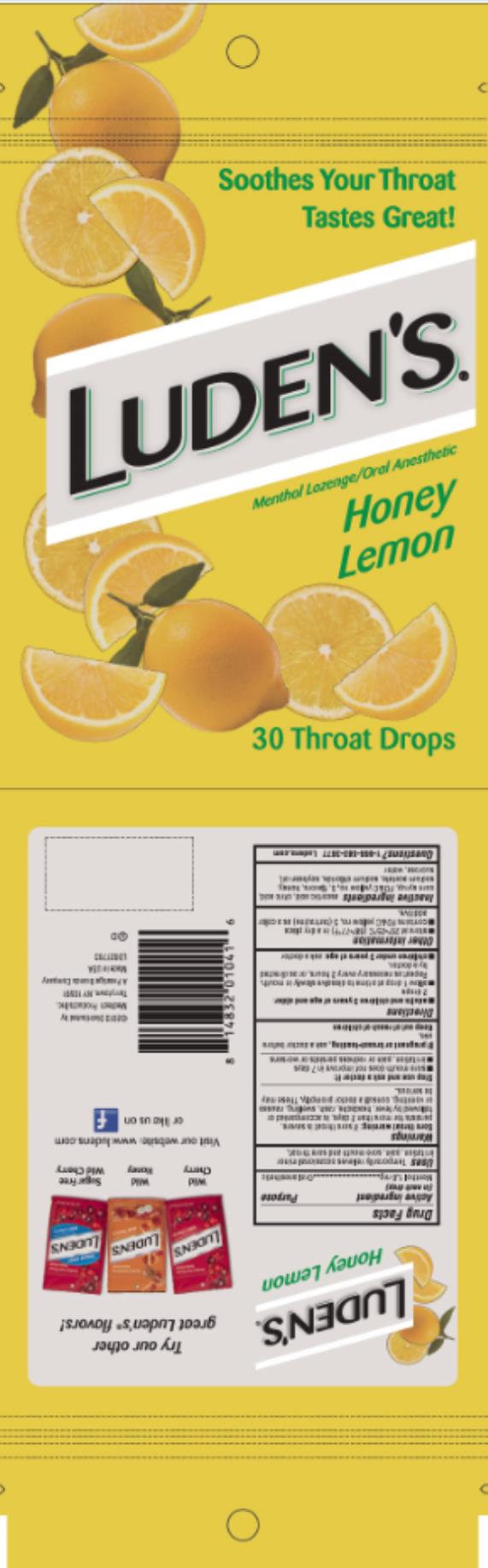 DRUG LABEL: Ludens Honey Licorice Throat Drops
NDC: 52183-255 | Form: LOZENGE
Manufacturer: Prestige Brands Holdings, Inc.
Category: otc | Type: HUMAN OTC DRUG LABEL
Date: 20200630

ACTIVE INGREDIENTS: MENTHOL 1.6 mg/1 1
INACTIVE INGREDIENTS: CORN SYRUP; SODIUM ACETATE; SOYBEAN OIL; SUCROSE; GLYCERIN; HONEY

Ludens Menthol Throat Lozenges

Luden’s Original Menthol Throat Drops

Drug Facts

Active ingredient (in each drop)

Menthol 2.5 mg

Purpose

Oral anesthetic

Uses

- temporarily relieves: occasional minor irritation, pain, sore mouth, and sore throat

Warnings

Sore throat warning: if sore throat is severe, persists for more than 2 days, is accompanied or followed by fever, headache, rash, swelling, nausea or vomiting, consult a doctor promptly. These may be serious.

Stop use and ask a doctor if:

- sore mouth does not improve in 7 days
- irritation, pain or redness lasts or worsens.

If pregnant or breast-feeding,

ask a doctor before use.

Directions

- adults and children 3 years of age and older: allow drop to dissolve slowly in mouth. Repeat as necessary every 2 hours, or as directed by doctor.
- children under 3 years of age: ask a doctor

Other information

- store at 20-25ºC (68-77ºF) in a dry place
- Do not use if clear outer wrap is opened or missing.

Inactive ingredients

Caramel Color, Corn Syrup, Flavors, Sodium Acetate, Soybean Oil used as a processing aid, Sucrose, Water

Questions or comments?

Call 1-866-583-3677
Luden’s Honey Licorice Throat Drops

Drug Facts

Active ingredient (in each drop)

Menthol 1.0 mg

Purpose

Oral anesthetic

Uses

- temporarily relieves: occasional minor irritation, pain, sore mouth, and sore throat

Warnings

Sore throat warning: if sore throat is severe, persists for more than 2 days, is accompanied or followed by fever, headache, rash, swelling, nausea or vomiting, consult a doctor promptly. These may be serious.

Stop use and ask a doctor if

- sore mouth does not improve in 7 days
- irritation, pain or redness lasts or worsens

If pregnant or breast-feeding,

ask a doctor before use.

Directions

- adults and children 3 years of age and older: allow 2 drops to dissolve slowly in mouth. Repeat as necessary every 2 hours, or as directed by a doctor.
- children under 3 years of age: ask a doctor

Other information

- store at 20-25ºC (68-77ºF) in a dry place
- do not use if clear outer wrap is opened or missing.

Inactive ingredients

Caramel Color, Corn Syrup, Flavors, Glycerin, Honey, Sodium Acetate, Soybean Oil used as a processing aid, Sucrose, Water

Questions or comments?

call 1-866-583-3677
Luden’s Honey Licorice Throat Drops

Drug Facts

Active ingredient (in each drop)

Menthol 1.6 mg

Purpose

Oral anesthetic

Uses

- for temporary relief of occasional minor irritation, pain, sore mouth, and sore throat

Warnings

Sore throat warning: if sore throat is severe, persists for more than 2 days, is accompanied or followed by fever, headache, rash, swelling, nausea or vomiting, consult a doctor promptly. These may be serious.

Stop use and ask a doctor if

- sore mouth does not improve in 7 days
- irritation, pain or redness persists or worsens.

If pregnant or breast-feeding,

ask a health professional before use.

Directions

- Adults and children 3 years of age and older:
- allow 1 drop at a time to dissolve slowly in mouth. Repeat as necessary every 2 hours, or as directed by a doctor.
- Children under 3 years of age: ask a doctor

Other information

- store at 20-25ºC (68-77ºF) in a dry place

Inactive ingredients

caramel color, corn syrup, flavors, glycerin, honey, sodium acetate, soybean oil, sucrose.

Questions?

1-866-583-3677 Ludens.com

Luden’s Honey Lemon Throat Drops

Drug Facts

Active ingredient (in each drop)

Menthol 1.0 mg

Purpose

Oral anesthetic

Uses

- temporarily relieves: occasional minor irritation, pain, sore mouth, and sore throat

Warnings

Sore throat warning: if sore throat is severe, persists for more than 2 days, is accompanied or followed by fever, headache, rash, swelling, nausea or vomiting, consult a doctor promptly. These may be serious.

Stop use and ask a doctor if

- sore mouth does not improve in 7 days
- irritation, pain or redness lasts or worsens

If pregnant or breast-feeding,

ask a doctor before use.

Directions

- adults and children 3 years of age and older: allow 2 drops to dissolve slowly in mouth. Repeat as necessary every 2 hours, or as directed by a doctor.
- children under 3 years of age: ask a doctor

Other information

- store at 20-25ºC (68-77ºF) in a dry place
- do not use if clear outer wrap is opened or missing.
- contains FD&C yellow no. 5 (tartrazine) as a color additive

Inactive ingredients

ascorbic acid, citric acid, corn syrup, FD&C yellow 5, flavors, honey, sodium acetate, sodium chloride, soybean oil, sucrose

Questions?

1-866-583-3677 Ludens.com

Luden’s Honey Lemon Throat Drops

Drug Facts

Active ingredient (in each drop)

Menthol 1.6 mg

Purpose

Oral anesthetic

Uses

- for temporary relief of occasional minor irritation, pain, sore mouth, and sore throat

Warnings

Sore throat warning: if sore throat is severe, persists for more than 2 days, is accompanied or followed by fever, headache, rash, swelling, nausea or vomiting, consult a doctor promptly. These may be serious.

Stop use and ask a doctor if

- sore mouth does not improve in 7 days
- irritation, pain or redness persists or worsens.

If pregnant or breast-feeding,

ask a health professional before use.

Directions

- Adults and children 3 years of age and older: 2 drops.
- allow 1 drop at a time to dissolve slowly in mouth. Repeat as necessary every 2 hours, or as directed by a doctor.
- Children under 3 years of age: ask a doctor

Other information

- store at 20-25ºC (68-77ºF) in a dry place
- contains FD&C yellow no. 5 (tartrazine) as a color additive

Inactive ingredients

caramel color, corn syrup, flavors, glycerin, honey, sodium acetate, soybean oil, sucrose.

Questions?

1-866-583-3677 Ludens.com

PRINCIPAL DISPLAY PANEL

LUDEN’S
ORIGINAL MENTHOL
Menthol lozenge
Oral Anesthetic
14 Drops

Principal Display Panel

LUDEN’S
HONEY LICORICE
Menthol lozenge/Oral Anesthetic
20 Drops

Principal Display Panel

LUDEN’S
HONEY LICORICE
Menthol lozenge
Oral Anesthetic
30 Drops

Principal Display Panel

LUDEN’S
HONEY LEMON
Menthol lozenge
Oral Anesthetic
14 Drops

Principal Display Panel

LUDEN’S
HONEY LEMON
Menthol lozenge
Oral Anesthetic
30 Drops